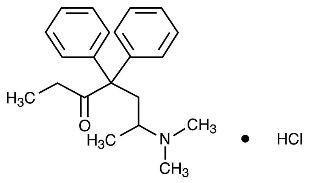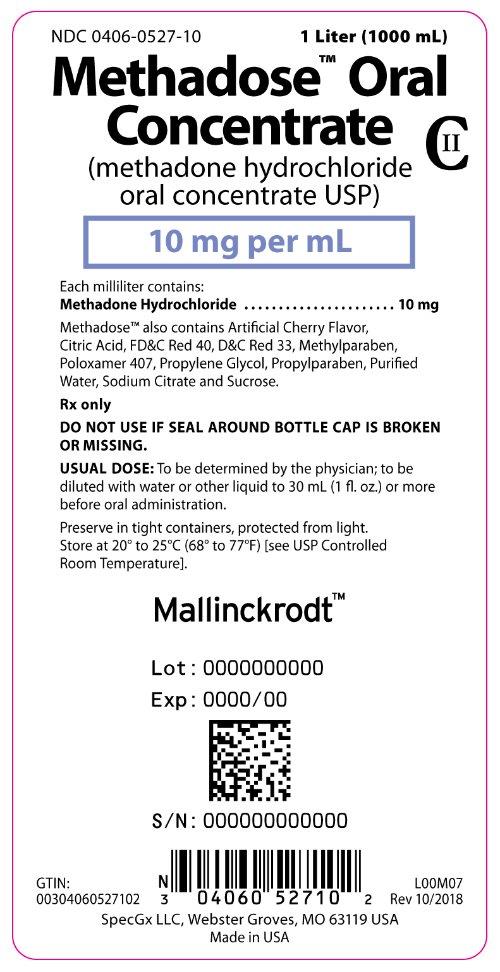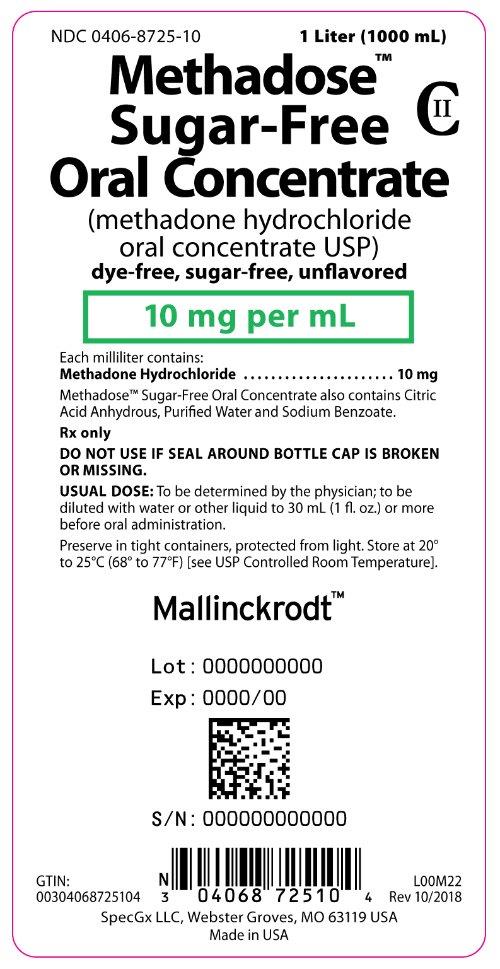 DRUG LABEL: METHADOSE
NDC: 0406-0527 | Form: CONCENTRATE
Manufacturer: SpecGx LLC
Category: prescription | Type: HUMAN PRESCRIPTION DRUG LABEL
Date: 20251222
DEA Schedule: CII

ACTIVE INGREDIENTS: METHADONE HYDROCHLORIDE 10 mg/1 mL
INACTIVE INGREDIENTS: ANHYDROUS CITRIC ACID; FD&C RED NO. 40; D&C RED NO. 33; METHYLPARABEN; POLOXAMER 407; PROPYLENE GLYCOL; PROPYLPARABEN; WATER; TRISODIUM CITRATE DIHYDRATE; SUCROSE

HIGHLIGHTS OF PRESCRIBING INFORMATION

These highlights do not include all the information needed to use METHADOSE safely and effectively. See full prescribing information for METHADOSE.
METHADOSE (methadone hydrochloride) oral concentrate, CII
Initial U.S. Approval: 1947

WARNING: LIFE-THREATENING RESPIRATORY DEPRESSION, LIFE-THREATENING QT PROLONGATION, ACCIDENTAL INGESTION, ABUSE POTENTIAL, INTERACTIONS WITH DRUGS AFFECTING CYTOCHROME P450 ISOENZYMES and TREATMENT FOR OPIOID ADDICTION

See full prescribing information for complete boxed warning.

- Fatal respiratory depression may occur, with highest risk at initiation and with dose increases. Instruct patients on proper administration of METHADOSE to reduce the risk. (5.1)
- Concomitant use with benzodiazepines or other central nervous system (CNS) depressants, including alcohol, may result in profound sedation, respiratory depression, and death. (5.2, 7)
- QT Interval prolongation and serious arrhythmia (torsades de pointes) have occurred with treatment with methadone. (5.3)
- Accidental ingestion of METHADOSE can result in fatal overdose of methadone, especially in children. (5.4)
- METHADOSE contains methadone, a Schedule II controlled substance and can be abused and criminally diverted. (5.5)
- Concomitant use with CYP3A4, 2B6, 2C19, 2C9 or 2D6 inhibitors or discontinuation of concomitantly used CYP3A4, 2B6, 2C19, or 2C9 inducers can result in a fatal overdose of methadone. (5.7, 7)
- Methadone products, when used for the treatment of opioid addiction in detoxification or maintenance programs, shall be dispensed only by certified opioid treatment programs as stipulated in 42 CFR 8.12. (2.1)

RECENT MAJOR CHANGES

Dosage and Administration (2.3, 2.6) | 12/2025
Warnings and Precautions (5.1, 5.2, 5.13, 5.15) | 12/2025

1 INDICATIONS AND USAGE

METHADOSE is an opioid agonist indicated for the:

- Detoxification treatment of opioid addiction (heroin or other morphine-like drugs). (1)
- Maintenance treatment of opioid addiction (heroin or other morphine-like drugs), in conjunction with appropriate social and medical services. (1)

Limitations of Use

- Methadone products used for the treatment of opioid addiction in detoxification or maintenance programs are subject to the conditions for distribution and use required under 21 CFR, Title 42, Sec. 8. (1, 2.1)

2 DOSAGE AND ADMINISTRATION

- Strongly consider recommending or prescribing an opioid overdose reversal agent (e.g., naloxone, nalmefene) at the time METHADOSE is initiated or renewed because patients being treated with methadone may be at risk for opioid overdose during initiation or titration, or in the case of relapse to illicit use. (2.3)
- Initiation of Detoxification and Maintenance Treatment: A single dose of 20 to 30 mg may be sufficient to suppress withdrawal syndrome. (2.4)
- Maintenance Treatment: Clinical stability is most commonly achieved at doses between 80 to 120 mg/day. (2.5)
- Do not rapidly reduce or abruptly discontinue METHADOSE in a physically-dependent patient. (2.6, 5.15)

3 DOSAGE FORMS AND STRENGTHS

Oral concentrate: 10 mg/mL in 1-Liter bottle (3)

4 CONTRAINDICATIONS

- Significant respiratory depression (4)
- Acute or severe bronchial asthma (4)
- Known or suspected paralytic ileus (4)
- Known hypersensitivity to methadone (4)

5 WARNINGS AND PRECAUTIONS

- Neonatal Opioid Withdrawal Syndrome: Neonatal opioid withdrawal syndrome (NOWS) is an expected and treatable outcome of prolonged use of opioids during pregnancy. (5.6)
- Life-Threatening Respiratory Depression in Patients with Chronic Pulmonary Disease or in Elderly, Cachectic, or Debilitated Patients: Monitor closely, particularly during initiation and titration. (5.8)
- Serotonin Syndrome: Potentially life-threatening condition could result from concomitant serotonergic drug administration. Discontinue METHADOSE if serotonin syndrome is suspected. (5.9)
- Adrenal Insufficiency: If diagnosed, treat with physiologic replacement of corticosteroids, and wean patient off of the opioid. (5.10)
- Severe Hypotension: Monitor during dose initiation and titration. (5.11)
- Risks of Use in Patients with Head Injury and Increased Intracranial Pressure: Monitor for sedation and respiratory depression. Avoid use of methadone in patients with impaired consciousness or coma susceptible to intracranial effects of CO2 retention. (5.12)

6 ADVERSE REACTIONS

Most Common Adverse Reactions Are: lightheadedness, dizziness, sedation, nausea, vomiting, and sweating. (6)

To report SUSPECTED ADVERSE REACTIONS, contact Mallinckrodt at 1-800-778-7898 or FDA at 1-800-FDA-1088 or www.fda.gov/medwatch.

7 DRUG INTERACTIONS

- Potentially Arrhythmogenic Agents: Monitor patients closely for cardiac conduction changes. (7)
- Interactions with CNS Depressants: Consider dose reduction of one or both drugs because of additive effects. (7)
- Mixed Agonist/Antagonist and Partial Agonist Opioids: Avoid concomitant use with METHADOSE because it may precipitate withdrawal symptoms. (5.15, 7)

8 USE IN SPECIFIC POPULATIONS

- Lactation: Monitor breastfed infants for increased drowsiness and breathing difficulties. (8.2)

FULL PRESCRIBING INFORMATION

WARNING: LIFE-THREATENING RESPIRATORY DEPRESSION, LIFE-THREATENING QT PROLONGATION, ACCIDENTAL INGESTION, ABUSE POTENTIAL, INTERACTIONS WITH DRUGS AFFECTING CYTOCHROME P450 ISOENZYMES and TREATMENT FOR OPIOID ADDICTION

Life-Threatening Respiratory Depression
Respiratory depression, including fatal cases, have been reported during initiation and conversion of patients to methadone, and even when the drug has been used as recommended and not misused or abused [see Warnings and Precautions (5.1)]. Proper dosing and titration are essential and METHADOSE should only be prescribed by healthcare professionals who are knowledgeable in the use of methadone for detoxification and maintenance treatment of opioid addiction. Monitor for respiratory depression, especially during initiation of METHADOSE or following a dose increase. The peak respiratory depressant effect of methadone occurs later, and persists longer than the peak pharmacologic effect, especially during the initial dosing period.

Managing Risks from Concomitant Use with Benzodiazepines or Other CNS Depressants
Concomitant use with benzodiazepines or other central nervous system (CNS) depressants, including alcohol, is a risk factor for respiratory depression and death [see Warnings and Precautions (5.2)].

- Reserve concomitant prescribing of benzodiazepines or other CNS depressants in patients in methadone treatment to those for whom alternatives to benzodiazepines or other CNS depressants are inadequate.
- Follow patients for signs and symptoms of respiratory depression and sedation. If the patient is visibly sedated, evaluate the cause of sedation and consider delaying or omitting daily methadone dosing.

Life-Threatening QT Prolongation
QT interval prolongation and serious arrhythmia (torsades de pointes) have occurred during treatment with methadone [see Warnings and Precautions (5.3)]. Most cases involve patients being treated for pain with large, multiple daily doses of methadone, although cases have been reported in patients receiving doses commonly used for maintenance treatment of opioid addiction. Closely monitor patients with risk factors for development of prolonged QT interval, a history of cardiac conduction abnormalities, and those taking medications affecting cardiac conduction for changes in cardiac rhythm during initiation and titration of METHADOSE.

Accidental Ingestion
Accidental ingestion of METHADOSE, especially by children, can result in fatal overdose of methadone [see Warnings and Precautions (5.4)].

Misuse, Abuse, and Diversion of Opioids
METHADOSE contains methadone, an opioid agonist and Schedule II controlled substance with an abuse liability similar to other opioid agonists, legal or illicit [see Warnings and Precautions (5.5)].

Interactions with Drugs Affecting Cytochrome P450 Isoenzymes
The concomitant use of METHADOSE with all cytochrome P450 3A4, 2B6, 2C19, 2C9 or 2D6 inhibitors may result in an increase in methadone plasma concentrations, which could cause potentially fatal respiratory depression. In addition, discontinuation of concomitantly used cytochrome P450 3A4 2B6, 2C19, or 2C9 inducers may also result in an increase in methadone plasma concentration. Follow patients closely for respiratory depression and sedation, and consider dosage reduction with any changes of concomitant medications that can result in an increase in methadone levels [see Warnings and Precautions (5.7), Drug Interactions (7)].
Conditions for Distribution and Use of Methadone Products for the Treatment of Opioid Addiction
For detoxification and maintenance of opioid dependence, methadone should be administered in accordance with the treatment standards cited in 42 CFR Section 8, including limitations on unsupervised administration [see Dosage and Administration (2.1)].

RECENT MAJOR CHANGES

Boxed Warning 01/2017

Warnings and Precautions (5) 01/2017

1 INDICATIONS AND USAGE

METHADOSE contains methadone, an opioid agonist indicated for the:

- detoxification treatment of opioid addiction (heroin or other morphine-like drugs).
- maintenance treatment of opioid addiction (heroin or other morphine-like drugs), in conjunction with appropriate social and medical services.

Limitations of Use
Methadone products used for the treatment of opioid addiction in detoxification or maintenance programs are subject to the conditions for distribution and use required under 21 CFR, Title 42, Sec 8 [see Dosage and Administration (2.1)].

2 DOSAGE AND ADMINISTRATION

2.1 Conditions for Distribution and Use of Methadone Products for the Treatment of Opioid Addiction

Code of Federal Regulations, Title 42, Sec 8: Methadone products when used for the treatment of opioid addiction in detoxification or maintenance programs, shall be dispensed only by opioid treatment programs (and agencies, practitioners or institutions by formal agreement with the program sponsor) certified by the Substance Abuse and Mental Health Services Administration and approved by the designated state authority. Certified treatment programs shall dispense and use methadone in oral form only and according to the treatment requirements stipulated in the Federal Opioid Treatment Standards (42 CFR 8.12). See below for important regulatory exceptions to the general requirement for certification to provide opioid agonist treatment.

Failure to abide by the requirements in these regulations may result in criminal prosecution, seizure of the drug supply, revocation of the program approval, and injunction precluding operation of the program.

Regulatory Exceptions to the General Requirement for Certification to Provide Opioid Agonist Treatment

- During inpatient care, when the patient was admitted for any condition other than concurrent opioid addiction (pursuant to 21 CFR 1306.07(c)), to facilitate the treatment of the primary admitting diagnosis.
- During an emergency period of no longer than 3 days while definitive care for the addiction is being sought in an appropriately licensed facility (pursuant to 21 CFR 1306.07(b)).

2.2 Important Dosage and Administration Information

METHADOSE is for oral administration only. The preparation must not be injected. Package in child-resistant containers and inform patients that METHADOSE should be kept out of reach of children to prevent accidental ingestion.

Consider the following important factors that differentiate methadone from other opioids:

- The peak respiratory depressant effect of methadone occurs later and persists longer than its peak pharmacologic effect.
- A high degree of opioid tolerance does not eliminate the possibility of methadone overdose, iatrogenic or otherwise. Deaths have been reported during conversion to methadone from chronic, high-dose treatment with other opioid agonists and during initiation of methadone treatment of addiction in subjects previously abusing high doses of other opioid agonists.
- There is high interpatient variability in absorption, metabolism, and relative analgesic potency. Population-based conversion ratios between methadone and other opioids are not accurate when applied to individuals.
- With repeated dosing, methadone is retained in the liver and then slowly released, prolonging the duration of potential toxicity.
- Steady-state plasma concentrations are not attained until 3 to 5 days after initiation of dosing.

METHADOSE has a narrow therapeutic index, especially when combined with other drugs.

2.3 Patient Access to an Opioid Overdose Reversal Agent for the Emergency Treatment of Opioid Overdose

Inform patients and caregivers about opioid overdose reversal agents (e.g., naloxone, nalmefene) and discuss the importance of having access to an opioid overdose reversal agent. Because patients being treated with methadone may be at risk for opioid overdose during initiation or titration, or in the case of relapse to illicit use, strongly consider recommending or prescribing an overdose reversal agent for the emergency treatment of opioid overdose, both when initiating and renewing treatment with METHADOSE. Also consider recommending or prescribing such an agent if the patient has household members (including children) or other close contacts at risk for accidental ingestion or opioid overdose [see Warnings and Precautions (5.1)].

Discuss the options for obtaining an opioid overdose reversal agent (e.g., prescription, over-the-counter, or as part of a community-based program) [see Warnings and Precautions (5.1)].

There are important differences among the opioid overdose reversal agents, such as route of administration, product strength, approved patient age range, and pharmacokinetics. Be familiar with these differences, as outlined in the approved labeling for those products, prior to recommending or prescribing such an agent.

Advise patients and caregivers that opioid overdose reversal agents, such as naloxone or nalmefene may also be administered for a known or suspected overdose with METHADOSE itself [see Overdosage (10)].

2.4 Induction/Initial Dosing for Detoxification and Maintenance Treatment of Opioid Addiction

For detoxification and maintenance of opiate dependence, methadone should be administered in accordance with the treatment standards cited in 42 CFR Section 8.12, including limitations on unsupervised administration.

Administer the initial methadone dose under supervision, when there are no signs of sedation or intoxication, and the patient shows symptoms of withdrawal. An initial single dose of 20 to 30 mg of methadone will often be sufficient to suppress withdrawal symptoms. The initial dose should not exceed 30 mg.

To make same-day dosing adjustments, have the patient wait 2 to 4 hours for further evaluation, when peak levels have been reached. Provide an additional 5 to 10 mg of methadone if withdrawal symptoms have not been suppressed or if symptoms reappear.

The total daily dose of methadone on the first day of treatment should not ordinarily exceed 40 mg. Adjust the dose over the first week of treatment based on control of withdrawal symptoms at the time of expected peak activity (i.e., 2 to 4 hours after dosing). When adjusting the dose, keep in mind that methadone will accumulate over the first several days of dosing; deaths have occurred in early treatment due to the cumulative effects. Instruct patients that the dose will “hold” for a longer period of time as tissue stores of methadone accumulate.

Use lower initial doses for patients whose tolerance is expected to be low at treatment entry. Any patient who has not taken opioids for more than 5 days may no longer be tolerant. Do not determine initial doses based on previous treatment episodes or dollars spent per day on illicit drug use. Also consider concurrent medications and the general condition and medical status of the patient when selecting the initial dose.

During the induction phase of methadone maintenance treatment, patients are being withdrawn from other opioids and may show typical withdrawal symptoms. Monitor patients for signs and symptoms of opioid withdrawal including: lacrimation, rhinorrhea, sneezing, yawning, excessive perspiration, goose-flesh, fever, chilliness alternating with flushing, restlessness, irritability, weakness, anxiety, depression, dilated pupils, tremors, tachycardia, abdominal cramps, body aches, involuntary twitching and kicking movements, anorexia, nausea, vomiting, diarrhea, intestinal spasms, and weight loss and consider dose adjustment as indicated.

Short-Term Detoxification
For a brief course of stabilization followed by a period of medically supervised withdrawal, titrate the patient to a total daily dose of about 40 mg in divided doses to achieve an adequate stabilizing level. After 2 to 3 days of stabilization, gradually decrease the dose of methadone. Decrease the dose of methadone on a daily basis or at 2-day intervals, keeping the amount of methadone sufficient to keep withdrawal symptoms at a tolerable level. Hospitalized patients may tolerate a daily reduction of 20% of the total daily dose. Ambulatory patients may need a slower schedule.

2.5 Titration and Maintenance Treatment of Opioid Dependence

Titrate patients in maintenance treatment to a dose that prevents opioid withdrawal symptoms for 24 hours, reduces drug hunger or craving, and blocks or attenuates the euphoric effects of self-administered opioids, ensuring that the patient is tolerant to the sedative effects of methadone. Most commonly, clinical stability is achieved at doses between 80 to 120 mg/day. During prolonged administration of methadone, monitor patients for persistent constipation and manage accordingly.

2.6 Medically Supervised Withdrawal After a Period of Maintenance Treatment for Opioid Addiction

There is considerable variability in the appropriate rate of methadone taper in patients choosing medically supervised withdrawal from methadone treatment. Dose reductions should generally be less than 10% of the established tolerance or maintenance dose, and 10- to 14-day intervals should elapse between dose reductions. Apprise patients of the high risk of relapse to illicit drug use associated with discontinuation of methadone maintenance treatment. Do not rapidly reduce or abruptly discontinue METHADOSE in patients who may be physically dependent on opioids [see Warnings and Precautions (5.15)].

2.7 Risk of Relapse in Patients on Methadone Maintenance Treatment of Opioid Addiction

Abrupt opioid discontinuation can lead to development of opioid withdrawal symptoms [see Drug Abuse and Dependence (9.3)]. Opioid withdrawal symptoms have been associated with an increased risk of relapse to illicit drug use in susceptible patients.

2.8 Considerations for Management of Acute Pain During Methadone Maintenance Treatment

Patients in methadone maintenance treatment for opioid dependence who experience physical trauma, postoperative pain, or other acute pain cannot be expected to derive analgesia from their existing dose of methadone. Such patients should be administered analgesics, including opioids, in doses that would otherwise be indicated for non-methadone-treated patients with similar painful conditions. When opioids are required for management of acute pain in methadone maintenance patients, somewhat higher and/or more frequent doses will often be required than would be the case for non-tolerant patients due to the opioid tolerance induced by methadone.

2.9 Dosage Adjustment During Pregnancy

Methadone clearance may be increased during pregnancy. During pregnancy, a woman’s methadone dose may need to be increased or the dosing interval decreased [see Use in Specific Populations (8.1)].

3 DOSAGE FORMS AND STRENGTHS

Oral Concentrate:

- 10 mg methadone hydrochloride (equivalent to 8.95 mg of methadone) per mL (10 mg/mL) as a red, cherry-flavored liquid concentrate in 1-liter bottles
- 10 mg methadone hydrochloride (equivalent to 8.95 mg of methadone) per mL (10 mg/mL) as a dye-free, sugar-free, unflavored, clear liquid concentrate in 1-liter bottles

4 CONTRAINDICATIONS

METHADOSE is contraindicated in patients with:

- Significant respiratory depression [see Warnings and Precautions (5.1)]
- Acute or severe bronchial asthma in an unmonitored setting or in the absence of resuscitative equipment [see Warnings and Precautions (5.8)]
- Known or suspected gastrointestinal obstruction, including paralytic ileus [see Warnings and Precautions (5.13)]
- Hypersensitivity (e.g., anaphylaxis) to methadone or any other ingredient in METHADOSE [see Adverse Reactions (6)]

5 WARNINGS AND PRECAUTIONS

5.1 Life-Threatening Respiratory Depression

Serious, life-threatening, or fatal respiratory depression has been reported with the use of methadone, even when used as recommended. Respiratory depression, if not immediately recognized and treated, may lead to respiratory arrest and death. Respiratory depression from opioids is manifested by a reduced urge to breathe and a decreased rate of respiration, often associated with a “sighing” pattern of breathing (deep breaths separated by abnormally long pauses). Carbon dioxide (CO2) retention from opioid-induced respiratory depression can exacerbate the sedating effects of opioids. Management of respiratory depression may include close observation, supportive measures, and use of opioid overdose reversal agents, depending on the patient’s clinical status [see Overdosage (10)].

While serious, life-threatening, or fatal respiratory depression can occur at any time during the use of METHADOSE, the risk is greatest during the initiation of therapy or following a dose increase. The peak respiratory depressant effect of methadone occurs later, and persists longer than the peak pharmacologic effect, especially during the initial dosing period. Monitor patients closely for respiratory depression, when initiating therapy with METHADOSE and following dose increases.

Instruct patients against use by individuals other than the patient for whom methadone was prescribed and to keep methadone out of the reach of children, as such inappropriate use may result in fatal respiratory depression [see Patient Counseling Information (17)].

To reduce the risk of respiratory depression, proper dosing and titration of methadone are essential [see Dosage and Administration (2.4)]. Overestimating the methadone dosage when initiating treatment can result in fatal overdose with the first dose.

To further reduce the risk of respiratory depression, consider the following:

- Patients tolerant to other opioids may be incompletely tolerant to methadone. Incomplete cross-tolerance is of particular concern for patients tolerant to other mu-opioid agonists. Deaths have been reported during conversion from chronic, high-dose treatment with other opioid agonists. Follow induction directions closely to avoid inadvertent overdose [see Dosage and Administration (2.4)].
- Proper dosing and titration are essential and methadone should be overseen only by healthcare professionals who are knowledgeable in the pharmacokinetics and pharmacodynamics of methadone.

Educate patients and caregivers on how to recognize respiratory depression and emphasize the importance of calling 911 or getting emergency medical help right away in the event of a known or suspected overdose [see Patient Counseling Information (17)].

Opioids can cause sleep-related breathing disorders including central sleep apnea (CSA) and sleep-related hypoxemia. Opioid use increases the risk of CSA in a dose-dependent fashion. In patients who present with CSA, consider decreasing the opioid dosage using best practices for opioid taper [see Dosage and Administration (2)].

Patient Access to an Opioid Overdose Reversal Agent for the Emergency Treatment of Opioid Overdose

Inform patients and caregivers about opioid overdose reversal agents (e.g., naloxone, nalmefene) and discuss the importance of having access to an opioid overdose reversal agent. Because patients being treated with methadone may be at risk for opioid overdose during initiation or titration, or in the case of relapse to illicit use, strongly consider recommending or prescribing an opioid overdose reversal agent for the emergency treatment of an opioid overdose, both when initiating and renewing treatment with METHADOSE. Also consider recommending or prescribing such an agent if the patient has household members (including children) or other close contacts at risk for accidental ingestion or opioid overdose [see Dosage and Administration (2.3)].

Discuss the options for obtaining an opioid overdose reversal agent (e.g., prescription, over-the-counter, or as part of a community-based program).

There are important differences among the opioid overdose reversal agents, such as route of administration, product strength, approved patient age range, and pharmacokinetics. Be familiar with these differences, as outlined in the approved labeling for those products, prior to recommending or prescribing such an agent.

Advise patients and caregivers that an opioid overdose reversal agent, such as naloxone or nalmefene, may also be administered for a known or suspected overdose with METHADOSE itself [see Overdosage (10)].

Educate patients and caregivers on how to recognize respiratory depression and how to use an opioid overdose reversal agent for the emergency treatment of opioid overdose. Emphasize the importance of calling 911 or getting emergency medical help, even if an opioid overdose reversal agent is administered.

5.2 Managing Risks from Concomitant Use of Benzodiazepines or Other CNS Depressants with Methadone

Concomitant use of methadone and benzodiazepines and/or other CNS depressants (e.g., alcohol, non-benzodiazepine sedative/hypnotics, anxiolytics, tranquilizers, muscle relaxants, general anesthetics, antipsychotics, gabapentinoids [gabapentin or pregabalin], and other opioids), increases the risk of adverse reactions including overdose and death. Medication-assisted treatment of opioid use disorder, however, should not be categorically denied to patients taking these drugs. Prohibiting or creating barriers to treatment can pose an even greater risk of morbidity and mortality due to the opioid use disorder alone.

As a routine part of orientation to methadone treatment, educate patients about the risks of concomitant use of benzodiazepines, sedatives, opioid analgesics, or alcohol.

Develop strategies to manage use of prescribed or illicit benzodiazepines or other CNS depressants at admission to methadone treatment, or if it emerges as a concern during treatment. Adjustments to induction procedures and additional monitoring may be required. There is no evidence to support dose limitations or arbitrary caps of methadone as a strategy to address benzodiazepine use in methadone-treated patients. However, if a patient is sedated at the time of methadone dosing, ensure that a medically-trained healthcare provider evaluates the cause of sedation and delays or omits the methadone dose if appropriate.

Cessation of benzodiazepines or other CNS depressants is preferred in most cases of concomitant use. In some cases monitoring in a higher level of care for taper may be appropriate. In others, gradually tapering a patient off a prescribed benzodiazepine or other CNS depressant or decreasing to the lowest effective dose may be appropriate.

For patients in methadone treatment, benzodiazepines are not the treatment of choice for anxiety or insomnia. Before co-prescribing benzodiazepines, ensure that patients are appropriately diagnosed and consider alternative medications and non-pharmacologic treatments to address anxiety or insomnia. Ensure that other healthcare providers prescribing benzodiazepines or other CNS depressants are aware of the patient’s methadone treatment and coordinate care to minimize the risks associated with concomitant use.

If concomitant use is warranted, strongly consider recommending or prescribing an opioid overdose reversal agent, as is recommended for all patients on methadone treatment for opioid use disorder [see Warnings and Precautions (5.1)].

In addition, take measures to confirm that patients are taking the medications prescribed and not diverting or supplementing with illicit drugs. Toxicology screening should test for prescribed and illicit benzodiazepines [see Drug Interactions (7)].

5.3 Life-Threatening QT Prolongation

Cases of QT interval prolongation and serious arrhythmia (torsades de pointes) have been observed during treatment with methadone. These cases appear to be more commonly associated with, but not limited to, higher dose treatment (> 200 mg/day). Most cases involve patients being treated for pain with large, multiple daily doses of methadone, although cases have been reported in patients receiving doses commonly used for maintenance treatment of opioid addiction. In most patients on the lower doses typically used for maintenance, concomitant medications and/or clinical conditions such as hypokalemia were noted as contributing factors. However, the evidence strongly suggests that methadone possesses the potential for adverse cardiac conduction effects in some patients. The effects of methadone on the QT interval have been confirmed in in vivo laboratory studies, and methadone has been shown to inhibit cardiac potassium channels in in vitro studies.

Closely monitor patients with risk factors for development of prolonged QT interval (e.g., cardiac hypertrophy, concomitant diuretic use, hypokalemia, hypomagnesemia), a history of cardiac conduction abnormalities, and those taking medications affecting cardiac conduction. QT prolongation has also been reported in patients with no prior cardiac history who have received high doses of methadone.

Evaluate patients developing QT prolongation while on METHADOSE treatment for the presence of modifiable risk factors, such as concomitant medications with cardiac effects, drugs which might cause electrolyte abnormalities, and drugs which might act as inhibitors of methadone metabolism.

Only initiate therapy with METHADOSE in patients for whom the anticipated benefit outweighs the risk of QT prolongation and development of dysrhythmias that have been reported with high doses of methadone. The use of methadone in patients already known to have a prolonged QT interval has not been systematically studied.

5.4 Accidental Ingestion

Accidental ingestion of even one dose of METHADOSE, especially by children, can result in respiratory depression and death due to an overdose. Keep METHADOSE out of reach of children to prevent accidental ingestion [see Warnings and Precautions (5.1)].

5.5 Misuse, Abuse, and Diversion of Opioids

METHADOSE contains methadone, an opioid agonist and a Schedule II controlled substance. Methadone can be abused in a manner similar to other opioid agonists, legal or illicit. Opioid agonists are sought by and people with opioid use disorders and are subject to criminal diversion.

Contact local state professional licensing board or state-controlled substances authority for information on how to prevent and detect abuse or diversion of this product.

5.6 Neonatal Opioid Withdrawal Syndrome

Neonatal opioid withdrawal syndrome (NOWS) is an expected and treatable outcome of prolonged use of opioids during pregnancy, whether that use is medically-authorized or illicit. Unlike opioid withdrawal syndrome in adults, NOWS may be life-threatening if not recognized and treated in the neonate. Healthcare professionals should observe newborns for signs of NOWS and manage accordingly [see Use in Specific Populations (8.1)].

Advise pregnant women receiving opioid addiction treatment with METHADOSE of the risk of neonatal opioid withdrawal syndrome and ensure that appropriate treatment will be available [see Use in Specific Populations (8.1)]. This risk must be balanced against the risk of untreated opioid addiction which often results in continued or relapsing illicit opioid use and is associated with poor pregnancy outcomes. Therefore, prescribers should discuss the importance and benefits of management of opioid addiction throughout pregnancy.

5.7 Risks of Concomitant Use of Cytochrome P450 3A4, 2B6, 2C19, 2C9, or 2D6 Inhibitors or Discontinuation of P450 3A4, 2B6, 2C19, or 2C9 Inducers

Concomitant use of METHADOSE with CYP3A4, CYP2B6, CYP2C19, CYP2C9, or CYP2D6 inhibitors, may increase plasma concentrations of methadone, prolong opioid adverse reactions, and may cause potentially fatal respiratory depression, particularly when an inhibitor is added after a stable dose of METHADOSE is achieved. Similarly, discontinuation of concomitant CYP3A4, CYP2B6, CYP2C19, or CYP2C9 inducers in METHADOSE-treated patients may increase methadone plasma concentrations resulting in fatal respiratory depression. Consider dosage reduction of METHADOSE when using concomitant CYP3A4, CYP2B6, CYP2C19, CYP2C9 or CYP2D6 inhibitors or discontinuing CYP3A4, CYP2B6, CYP2C19, or CYP2C9 inducers in methadone-treated patients, and follow patients closely at frequent intervals for signs and symptoms of respiratory depression and sedation [see Drug Interactions (7)].

Addition of CYP3A4, CYP2B6, CYP2C19, or CYP2C9 inducers or discontinuation of a CYP3A4, CYP2B6, CYP2C19, CYP2C9, or CYP2D6 inhibitors in patients treated with METHADOSE may decrease methadone plasma concentrations, reducing efficacy and may lead to opioid withdrawal symptoms in patients physically dependent on methadone. When using METHADOSE with CYP3A4, CYP2B6, CYP2C19, or CYP2C9 inducers or discontinuing CYP3A4, CYP2B6, CYP2C19, CYP2C9, or CYP2D6 inhibitors, follow patients for signs or symptoms of opioid withdrawal and consider increasing the METHADOSE dosage as needed [see Drug Interactions (7)].

5.8 Life-Threatening Respiratory Depression in Patients with Chronic Pulmonary Disease or in Elderly, Cachectic, or Debilitated Patients

The use of METHADOSE in patients with acute or severe bronchial asthma in an unmonitored setting or in the absence of resuscitative equipment is contraindicated.

Patients with Chronic Pulmonary Disease
METHADOSE-treated patients with significant chronic obstructive pulmonary disease or cor pulmonale, and those with a substantially decreased respiratory reserve, hypoxia, hypercapnia, or pre-existing respiratory depression are at increased risk of decreased respiratory drive including apnea, even at recommended dosages of METHADOSE [see Warnings and Precautions (5.1)].

Elderly, Cachectic, or Debilitated Patients
Life-threatening respiratory depression is more likely to occur in elderly, cachectic, or debilitated patients because they may have altered pharmacokinetics or altered clearance compared to younger, healthier patients [see Warnings and Precautions (5.1)].

Monitor such patients closely, particularly when initiating and titrating METHADOSE and when METHADOSE is given concomitantly with other drugs that depress respiration [see Warnings and Precautions (5.2)].

5.9 Serotonin Syndrome with Concomitant Use of Serotonergic Drugs

Cases of serotonin syndrome, a potentially life-threatening condition, have been reported during concomitant use of METHADOSE with serotonergic drugs. Serotonergic drugs include selective serotonin reuptake inhibitors (SSRIs), serotonin and norepinephrine reuptake inhibitors (SNRIs), tricyclic antidepressants (TCAs), triptans, 5-HT3 receptor antagonists, drugs that affect the serotonergic neurotransmitter system (e.g., mirtazapine, trazodone, tramadol), certain muscle relaxants (i.e., cyclobenzaprine, metaxalone), and drugs that impair metabolism of serotonin (including MAO inhibitors, both those intended to treat psychiatric disorders and others, such as linezolid and intravenous methylene blue) [see Drug Interactions (7)]. This may occur within the recommended dosage range.

Serotonin syndrome symptoms may include mental status changes (e.g., agitation, hallucinations, coma), autonomic instability (e.g., tachycardia, labile blood pressure, hyperthermia), neuromuscular aberrations (e.g., hyperreflexia, incoordination, rigidity), and/or gastrointestinal symptoms (e.g., nausea, vomiting, diarrhea). The onset of symptoms generally occurs within several hours to a few days of concomitant use, but may occur later than that. Discontinue METHADOSE if serotonin syndrome is suspected.

5.10 Adrenal Insufficiency

Cases of adrenal insufficiency have been reported with opioid use, more often following greater than one month of use. Presentation of adrenal insufficiency may include non-specific symptoms and signs including nausea, vomiting, anorexia, fatigue, weakness, dizziness, and low blood pressure. If adrenal insufficiency is suspected, confirm the diagnosis with diagnostic testing as soon as possible. If adrenal insufficiency is diagnosed, treat with physiologic replacement doses of corticosteroids. Wean the patient off of the opioid to allow adrenal function to recover and continue corticosteroid treatment until adrenal function recovers. Other opioids may be tried as some cases reported use of a different opioid without recurrence of adrenal insufficiency. The information available does not identify any particular opioids as being more likely to be associated with adrenal insufficiency.

5.11 Severe Hypotension

Methadone may cause severe hypotension including orthostatic hypotension and syncope in ambulatory patients. There is an increased risk in patients whose ability to maintain normal blood pressure is compromised by a reduced blood volume or concurrent administration of certain CNS depressant drugs (e.g., phenothiazines or general anesthetics) [see Drug Interactions (7)]. Monitor these patients for signs of hypotension after initiating or titrating the dosage of METHADOSE. In patients with circulatory shock, METHADOSE may cause vasodilation that can further reduce cardiac output and blood pressure. Avoid the use of METHADOSE in patients with circulatory shock.

5.12 Risks of Use in Patients with Increased Intracranial Pressure, Brain Tumors, Head Injury, or Impaired Consciousness

In patients who may be susceptible to the intracranial effects of CO2 retention (e.g., those with evidence of increased intracranial pressure or brain tumors), METHADOSE may reduce respiratory drive, and the resultant CO2 retention can further increase intracranial pressure. Monitor such patients for signs of sedation and respiratory depression, particularly when initiating therapy with methadone. Opioids may also obscure the clinical course in a patient with a head injury.

Avoid the use of methadone in patients with impaired consciousness or coma.

5.13 Risks of Gastrointestinal Complications

METHADOSE is contraindicated in patients with known or suspected gastrointestinal obstruction, including paralytic ileus. The methadone in METHADOSE may cause spasm of the sphincter of Oddi. Opioids may cause increases in the serum amylase. Monitor patients with biliary tract disease, including acute pancreatitis, for worsening symptoms.

Cases of opioid-induced esophageal dysfunction (OIED) have been reported in patients taking opioids. The risk of OIED may increase as the dose and/or duration of opioids increases. Regularly evaluate patients for signs and symptoms of OIED (e.g., dysphagia, regurgitation, non-cardiac chest pain) and, if necessary, adjust opioid therapy as clinically appropriate [see Clinical Pharmacology (12.2)].

5.14 Increased Risks of Seizure in Patients with Seizure Disorders

Methadone may increase frequency of seizures in patients with seizure disorders and increase the risks of seizures occurring in other clinical settings associated with seizures. Monitor patients with a history of seizure disorders for worsened seizure control during METHADOSE therapy.

5.15 Withdrawal

Avoid the use of mixed agonist/antagonist (i.e., pentazocine, nalbuphine, and butorphanol) or partial agonist (e.g., buprenorphine) analgesics in patients who are receiving a full opioid agonist, including METHADOSE. In these patients, mixed agonists/antagonist and partial agonist analgesics may precipitate withdrawal symptoms [see Drug Interactions (7)].

When discontinuing METHADOSE, gradually taper the dosage [see Dosage and Administration (2.6, 2.7)]. Do not rapidly reduce or abruptly discontinue METHADOSE [see Drug Abuse and Dependence (9.3)].

5.16 Risks of Driving or Operating Machinery

METHADOSE may impair the mental or physical abilities needed to perform potentially hazardous activities such as driving a car or operating machinery. Warn patients not to drive or operate dangerous machinery unless they are tolerant to the effects of METHADOSE and know how they will react to the medication [see Patient Counseling Information (17)].

5.17 Hypoglycemia

Cases of methadone-associated hypoglycemia have been reported, some resulting in hospitalization. In many cases, patients had predisposing risk factors (e.g., diabetes). The relationship between methadone and hypoglycemia is not fully understood but may be dose dependent. If hypoglycemia is suspected, monitor blood glucose levels, and manage the patient as clinically appropriate.

5.18 Laboratory Test Interactions

False positive urine drug screens for methadone have been reported for several drugs including diphenhydramine, doxylamine, clomipramine, chlorpromazine, thioridazine, quetiapine, and verapamil.

6 ADVERSE REACTIONS

The following serious adverse reactions and/or conditions are described, or described in greater detail, in other sections:

- Respiratory Depression [see Warnings and Precautions (5.1)]
- Interactions with Benzodiazepines and other CNS Depressants [see Warnings and Precautions (5.2)]
- QT Prolongation [see Warnings and Precautions (5.3)]
- Serotonin Syndrome [see Warnings and Precautions (5.9)]
- Adrenal Insufficiency [see Warnings and Precautions (5.10)]
- Severe Hypotension [see Warnings and Precautions (5.11)]
- Gastrointestinal Adverse Reactions [see Warnings and Precautions (5.13)]
- Seizures [see Warnings and Precautions (5.14)]
- Withdrawal [see Warnings and Precautions (5.15)]
- Hypoglycemia [see Warnings and Precautions (5.17)]

The following adverse reactions have been identified during post-approval use of methadone. Because these reactions are reported voluntarily from a population of uncertain size, it is not always possible to reliably estimate their frequency or establish a causal relationship to drug exposure.

The major hazards of methadone are respiratory depression and, to a lesser degree, systemic hypotension. Respiratory arrest, shock, cardiac arrest, and death have occurred.

The most frequently observed adverse reactions include lightheadedness, dizziness, sedation, nausea, vomiting, and sweating. These effects seem to be more prominent in ambulatory patients and in those who are not suffering severe pain.

Other adverse reactions include the following:

Body as a Whole: asthenia (weakness), edema, headache

Cardiovascular: arrhythmias, bigeminal rhythms, bradycardia, cardiomyopathy, ECG abnormalities, extrasystoles, flushing, heart failure, hypotension, palpitations, phlebitis, QT interval prolongation, syncope, T-wave inversion, tachycardia, torsade de pointes, ventricular fibrillation, ventricular tachycardia

Central Nervous System: agitation, confusion, disorientation, dysphoria, euphoria, insomnia, hallucinations, seizures, visual disturbances, congenital oculomotor disorders (nystagmus, strabismus)

Endocrine: hypogonadism

Gastrointestinal: abdominal pain, anorexia, biliary tract spasm, constipation, dry mouth, glossitis

Hematologic: Reversible thrombocytopenia has been described in opioid addicts with chronic hepatitis.

Metabolic: hypokalemia, hypomagnesemia, weight gain

Musculoskeletal: decreased muscle mass and strength, osteoporosis and fractures

Renal: antidiuretic effect, urinary retention or hesitancy

Reproductive: amenorrhea, reduced libido and/or potency, reduced ejaculate volume, reduced seminal vesicle and prostate secretions, decreased sperm motility, abnormalities in sperm morphology

Respiratory: pulmonary edema, respiratory depression

Skin and Subcutaneous Tissue: pruritus, urticaria, other skin rashes, and rarely, hemorrhagic urticaria

Hypersensitivity: Anaphylaxis has been reported with ingredients contained in METHADOSE.

Serotonin syndrome: Cases of serotonin syndrome, a potentially life-threatening condition, have been reported during concomitant use of opioids with serotonergic drugs.

Adrenal insufficiency: Cases of adrenal insufficiency have been reported with opioid use, more often following greater than one month of use.

Androgen deficiency: Cases of androgen deficiency have occurred with chronic use of opioids [see Clinical Pharmacology (12.2)].

Hypoglycemia: Cases of hypoglycemia have been reported in patients taking methadone [see Warnings and Precautions (5.17)].

Opioid-induced esophageal dysfunction (OIED): Cases of OIED have been reported in patients taking opioids and may occur more frequently in patients taking higher doses of opioids, and/or in patients taking opioids longer term [see Warnings and Precautions (5.13)].

7 DRUG INTERACTIONS

Benzodiazepines and Other Central Nervous System (CNS) Depressants
Clinical Impact: | Due to additive pharmacologic effect, the concomitant use of benzodiazepines or other CNS depressants, including alcohol, increases the risk of respiratory depression, profound sedation, coma, and death.
Intervention: | Cessation of benzodiazepines or other CNS depressants is preferred in most cases of concomitant use. In some cases, monitoring in a higher level of care for taper may be appropriate. In others, gradually tapering a patient off of a prescribed benzodiazepine or other CNS depressant or decreasing to the lowest effective dose may be appropriate.; Before co-prescribing benzodiazepines for anxiety or insomnia, ensure that patients are appropriately diagnosed and consider alternative medications and non-pharmacologic treatments [see Warnings and Precautions (5.2)].; If concomitant use is warranted, strongly consider recommending or prescribing an opioid overdose reversal agent, as is recommended for all patients in treatment for opioid use disorder [see Warnings and Precautions (5.1)].
Examples: | Alcohol, benzodiazepines, and other sedatives/hypnotics, anxiolytics, tranquilizers, muscle relaxants, general anesthetics, antipsychotics, gabapentinoids (gabapentin or pregabalin), other opioids.
Inhibitors of CYP3A4, CYP2B6, CYP2C19, CYP2C9, or CYP2D6
Clinical Impact: | Methadone undergoes hepatic N-demethylation by several cytochrome P450 (CYP) isoforms, including CYP3A4, CYP2B6, CYP2C19, CYP2C9, and CYP2D6. The concomitant use of methadone and CYP3A4, CYP2B6, CYP2C19, CYP2C9, or CYP2D6 inhibitors can increase the plasma concentration of methadone, resulting in increased or prolonged opioid effects, and may result in a fatal overdose, particularly when an inhibitor is added after a stable dose of methadone is achieved. These effects may be more pronounced with concomitant use of drugs that inhibit more than one of the CYP enzymes listed above.; After stopping a CYP3A4, CYP2B6, CYP2C19, CYP2C9, or CYP2D6 inhibitor, as the effects of the inhibitor decline, the methadone plasma concentration can decrease [see Clinical Pharmacology (12.3)], resulting in decreased opioid efficacy or withdrawal symptoms in patients physically dependent on methadone.
Intervention: | If concomitant use is necessary, consider dosage reduction of methadone until stable drug effects are achieved. Monitor patients for respiratory depression and sedation at frequent intervals.; If a CYP3A4, CYP2B6, CYP2C19, CYP2C9, or CYP2D6 inhibitor is discontinued, follow patients for signs of opioid withdrawal and consider increasing the methadone dosage until stable drug effects are achieved.
Examples: | Macrolide antibiotics (e.g., erythromycin), azole-antifungal agents (e.g., ketoconazole), protease inhibitors (e.g., ritonavir), fluconazole, fluvoxamine, some selective serotonin reuptake inhibitors (SSRIs) (e.g., sertraline, fluvoxamine)
Inducers of CYP3A4, CYP2B6, CYP2C19, or CYP2C9
Clinical Impact: | The concomitant use of methadone and CYP3A4, CYP2B6, CYP2C19, or CYP2C9 inducers can decrease the plasma concentration of methadone [see Clinical Pharmacology (12.3)], resulting in decreased efficacy or onset of withdrawal symptoms in patients physically dependent on methadone. These effects could be more pronounced with concomitant use of drugs that can induce multiple CYP enzymes.; After stopping a CYP3A4, CYP2B6, CYP2C19, or CYP2C9 inducer, as the effects of the inducer decline, the methadone plasma concentration can increase [see Clinical Pharmacology (12.3)], which could increase or prolong both the therapeutic effects and adverse reactions, and may cause serious respiratory depression, sedation, or death.
Intervention: | If concomitant use is necessary, consider increasing the methadone dosage until stable drug effects are achieved. Monitor for signs of opioid withdrawal. If a CYP3A4, CYP2B6, CYP2C19, or CYP2C9 inducer is discontinued, consider methadone dosage reduction and monitor for signs of respiratory depression and sedation.
Examples: | Rifampin, carbamazepine, phenytoin, St. John’s Wort, Phenobarbital
Potentially Arrhythmogenic Agents
Clinical Impact: | Pharmacodynamic interactions may occur with concomitant use of methadone and potentially arrhythmogenic agents or drugs capable of inducing electrolyte disturbances (hypomagnesemia, hypokalemia).
Intervention: | Monitor patients closely for cardiac conduction changes.
Examples: | Drugs known to have potential to prolong QT interval: Class I and III antiarrhythmics, some neuroleptics and tricyclic antidepressants, and calcium channel blockers. Drugs capable of inducing electrolyte disturbances: Diuretics, laxatives, and, in rare cases, mineralocortocoid hormones.
Serotonergic Drugs
Clinical Impact: | The concomitant use of opioids with other drugs that affect the serotonergic neurotransmitter system has resulted in serotonin syndrome [see Warnings and Precautions (5.9)].
Intervention: | If concomitant use is warranted, carefully observe the patient, particularly during treatment initiation and dose adjustment. Discontinue METHADOSE if serotonin syndrome is suspected.
Examples: | Selective serotonin reuptake inhibitors (SSRIs), serotonin and norepinephrine reuptake inhibitors (SNRIs), tricyclic antidepressants (TCAs), triptans, 5-HT3 receptor antagonists, drugs that affect the serotonin neurotransmitter system (e.g., mirtazapine, trazodone, tramadol), certain muscle relaxants (i.e., cyclobenzaprine, metaxalone), monoamine oxidase (MAO) inhibitors (those intended to treat psychiatric disorders and also others, such as linezolid and intravenous methylene blue).
Monoamine Oxidase Inhibitors (MAOIs)
Clinical Impact: | MAOI interactions with opioids may manifest as serotonin syndrome or opioid toxicity (e.g., respiratory depression, coma) [see Warnings and Precautions (5.1, 5.9)].
Intervention: | The use of METHADOSE is not recommended for patients taking MAOIs or within 14 days of stopping such treatment.
Examples: | phenelzine, tranylcypromine, linezolid
Mixed Agonist/Antagonist and Partial Agonist Opioid Analgesics
Clinical Impact: | Patients maintained on methadone may experience withdrawal symptoms when given opioid antagonists, mixed agonist/antagonists, and partial agonists.
Intervention: | Avoid concomitant use.
Examples: | butorphanol, nalbuphine, pentazocine, buprenorphine
Muscle Relaxants
Clinical Impact: | Methadone may enhance the neuromuscular blocking action of skeletal muscle relaxants and produce an increased degree of respiratory depression.
Intervention: | Monitor patients for signs of respiratory depression that may be greater than otherwise expected and decrease the dosage of METHADOSE and/or the muscle relaxant as necessary. Due to the risk of respiratory depression with concomitant use of skeletal muscle relaxants and opioids, strongly consider recommending or prescribing an opioid overdose reversal agent, as is recommended for all patients in treatment for opioid use disorder [see Dosage and Administration (2.3), Warnings and Precautions (5.1, 5.2)].
Examples: | cyclobenzaprine, metaxalone
Diuretics
Clinical Impact: | Opioids can reduce the efficacy of diuretics by inducing the release of antidiuretic hormone.
Intervention: | Monitor patients for signs of diminished diuresis and/or effects on blood pressure and increase the dosage of the diuretic as needed.
Anticholinergic Drugs
Clinical Impact: | The concomitant use of anticholinergic drugs may increase risk of urinary retention and/or severe constipation, which may lead to paralytic ileus.
Intervention: | Monitor patients for signs of urinary retention or reduced gastric motility when METHADOSE is used concomitantly with anticholinergic drugs.

Paradoxical Effects of Anti-Retroviral Agents on Methadone
Concurrent use of certain protease inhibitors with CYP3A4 inhibitory activity, alone and in combination, such as abacavir, amprenavir, darunavir+ritonavir, efavirenz, nelfinavir, nevirapine, ritonavir, telaprevir, lopinavir+ritonavir, saquinavir+ritonavir, and tipranvir+ritonavir, has resulted in increased clearance or decreased plasma levels of methadone. This may result in reduced efficacy of METHADOSE and could precipitate a withdrawal syndrome. Monitor patients receiving METHADOSE and any of these anti-retroviral therapies closely for evidence of withdrawal effects and adjust the METHADOSE dose accordingly.

Effects of Methadone on Anti-Retroviral Agents
Didanosine and Stavudine
Experimental evidence demonstrated that methadone decreased the area under the concentration-time curve (AUC) and peak levels for didanosine and stavudine, with a more significant decrease for didanosine. Methadone disposition was not substantially altered.

Zidovudine
Experimental evidence demonstrated that methadone increased the AUC of zidovudine which could result in toxic effects.

Effects of Methadone on Antidepressants
Desipramine
Plasma levels of desipramine have increased with concurrent methadone administration.

8 USE IN SPECIFIC POPULATIONS

8.1 Pregnancy

Risk Summary
The majority of available data from clinical trials, observational studies, case series, and case reports on methadone use in pregnancy do not indicate an increased risk of major malformations specifically due to methadone.

Pregnant women involved in methadone maintenance programs have been reported to have improved prenatal care leading to reduced incidence of obstetric and fetal complications and neonatal morbidity and mortality when compared to women using illicit drugs. Several factors, including maternal use of illicit drugs, nutrition, infection and psychosocial circumstances, complicate the interpretation of investigations of the children of women who take methadone during pregnancy. Information is limited regarding dose and duration of methadone use during pregnancy, and most maternal exposure in these studies appears to occur after the first trimester of pregnancy (see Data).

Neonatal opioid withdrawal syndrome (NOWS) is an expected and treatable outcome of prolonged use of opioids during pregnancy [see Warnings and Precautions (5.6)].

In published animal reproduction studies, methadone administered subcutaneously during the early gestational period produced neural tube defects (i.e., exencephaly and cranioschisis) in the hamster at doses 2 times the human daily oral dose of 120 mg/day on a mg/m^2 basis (HDD) and in mice at doses equivalent to the HDD. Administration of methadone to pregnant animals during organogenesis and through lactation resulted decreased litter size, increased pup mortality, decreased pup body weights, developmental delays, and long-term neurochemical changes in the brain of offspring which correlate with altered behavioral responses that persist through adulthood at exposures comparable to and less than the HDD. Administration of methadone to male rodents prior to mating with untreated females resulted in increased neonatal mortality and significant differences in behavioral tests in the offspring at exposures comparable to and less than the HDD (see Data). Based on animal data, advise pregnant women of the potential risk to a fetus.

The estimated background risk of major birth defects and miscarriage for the indicated population is unknown. All pregnancies have a background risk of birth defect, loss, or other adverse outcomes. In the U.S. general population, the estimated background risk of major birth defects and miscarriage in clinically recognized pregnancies is 2% to 4% and 15% to 20%, respectively.

Clinical Considerations
Disease-Associated Maternal and Embryo-Fetal Risk
Untreated opioid addiction in pregnancy is associated with adverse obstetrical outcomes such as low birth weight, preterm birth, and fetal death. In addition, untreated opioid addiction often results in continued or relapsing illicit opioid use.

Dosage Adjustment During Pregnancy
Dosage adjustment using higher doses or administering the daily dose in divided doses may be necessary in pregnant women treated with Methadose. Pregnant women appear to have significantly lower trough plasma methadone concentrations, increased plasma methadone clearance, and shorter methadone half-life than after delivery [see Dosage and Administration (2.9), Clinical Pharmacology (12.3)]. Withdrawal signs and symptoms should be closely monitored and the dose adjusted as necessary.

Fetal/Neonatal Adverse Reactions
Neonatal opioid withdrawal syndrome may occur in newborn infants of mothers who are receiving treatment with METHADOSE.

Neonatal opioid withdrawal syndrome presents as irritability, hyperactivity and abnormal sleep pattern, high-pitched cry, tremor, vomiting, diarrhea, and/or failure to gain weight. Signs of neonatal withdrawal usually occur in the first days after birth. The duration and severity of neonatal opioid withdrawal syndrome may vary. Observe newborns for signs of neonatal opioid withdrawal syndrome and manage accordingly [see Warnings and Precautions (5.6)].

Labor or Delivery
Opioid-dependent women on methadone maintenance therapy may require additional analgesia during labor.

Monitor neonates exposed to opioid analgesics during labor for signs of excess sedation and respiratory depression.

Data
Human Data
The majority of available data from clinical trials, observational studies, case series, and case reports on methadone use in pregnancy do not indicate an increased risk of major malformations specifically due to methadone. Findings regarding specific major malformations, decreased fetal growth, premature birth and Sudden Infant Death Syndrome have been inconsistent. Children prenatally exposed to methadone have been reported to demonstrate mild but persistent deficits in performance on psychometric and behavioral tests and visual abnormalities.

In a multicenter, double-blind, randomized, controlled trial [Maternal Opioid Treatment: Human Experimental Research (MOTHER)] designed primarily to assess neonatal opioid withdrawal effects, opioid-dependent pregnant women were randomized to buprenorphine (n=86) or methadone (n=89) treatment, with enrollment at an average gestational age of 18.7 weeks in both groups. A total of 28 of the 86 women in the buprenorphine group (33%) and 16 of the 89 women in the methadone group (18%) discontinued treatment before the end of pregnancy.

Among women who remained in treatment until delivery, there was no difference between methadone-treated and buprenorphine-treated groups in the number of neonates requiring NOWS treatment or in the peak severity of NOWS. Buprenorphine-exposed neonates required less morphine (mean total dose, 1.1 mg vs. 10.4 mg), had shorter hospital stays (10.0 days vs. 17.5 days), and shorter duration of treatment for NOWS (4.1 days vs. 9.9 days) compared to the methadone-exposed group. There were no differences between groups in other primary outcomes (neonatal head circumference,) or secondary outcomes (weight and length at birth, preterm birth, gestational age at delivery, and
1-minute and 5-minute Apgar scores), or in the rates of maternal or neonatal adverse events. The outcomes among mothers who discontinued treatment before delivery and may have relapsed to illicit opioid use are not known. Because of the imbalance in discontinuation rates between the methadone and buprenorphine groups, the study findings are difficult to interpret.

Animal Data
Formal reproductive and developmental toxicology studies for methadone have not been conducted. Exposure margins for the following published study reports are based on a human daily dose (HDD) of 120 mg methadone using a body surface area comparison.

In a published study in pregnant hamsters, a single subcutaneous dose of methadone ranging from 31 mg/kg (2 times the HDD) to 185 mg/kg on Gestation Day 8 resulted in a decrease in the number of fetuses per litter and an increase in the percentage of fetuses exhibiting neural tube defects including exencephaly, cranioschisis, and “various other lesions.” The majority of the doses tested also resulted in maternal death. In a study in pregnant JBT/Jd mice, a single subcutaneous dose of 22 to 24 mg/kg methadone (approximately equivalent to the HDD) administered on Gestation Day 9 produced exencephaly in 11% of the embryos. In another study in pregnant mice, subcutaneous doses up to 28 mg/kg/day methadone (equivalent to the HDD) administered from Gestation Day 6 to 15 resulted in no malformations, but there were increased postimplantation loss and decreased live fetuses at 10 mg/kg/day or greater (0.4 times the HDD) and decreased ossification and fetal body weight at 20 mg/kg/day or greater (0.8 times the HDD). In a second study of pregnant mice dosed with subcutaneous doses up to 28 mg/kg/day methadone from Gestation Day 6 to 15, there was decreased pup viability, delayed onset of development of negative phototaxis and eye opening, increased righting reflexes at 5 mg/kg/day or greater (0.2 times the HDD), and decreased number of live pups at birth and decreased pup weight gain at 20 mg/kg/day or greater (0.8 times the HDD).

No effects were reported in a study of pregnant rats and rabbits at oral doses up to 40 mg/kg (3 and 6 times, respectively, the HDD) administered from Gestation Days 6 to 15 and 6 to 18, respectively.

When pregnant rats were treated with intraperitoneal doses of 2.5, 5, or 7.5 mg/kg methadone from one week prior to mating, through gestation until the end of lactation period, 5 mg/kg or greater (0.4 times the HDD) methadone resulted in decreases in litter size and live pups born and 7.5 mg/kg (0.6 times the HDD) resulted in decreased birth weights. Furthermore, decreased pup viability and pup body weight gain at 2.5 mg/kg or greater (0.2 times the HDD) were noted during the preweaning period.

Additional animal data demonstrate evidence for neurochemical changes in the brains of offspring from methadone-treated pregnant rats, including changes to the cholinergic, dopaminergic, noradrenergic, and serotonergic systems at doses below the HDD. Other animal studies have reported that prenatal and/or postnatal exposure to opioids including methadone alters neuronal development and behavior in the offspring including alterations in learning ability, motor activity, thermal regulation, nociceptive responses, and sensitivity to drugs at doses below the HDD. Treatment of pregnant rats subcutaneously with 5 mg/kg methadone from Gestation Day 14 to 19 (0.4 times the HDD) reduced fetal blood testosterone and androstenedione in males.

Published animal data have reported increased neonatal mortality in the offspring of male rodents that were treated with methadone at doses comparable to and less than the HDD for 1 to 12 days before and/or during mating (with more pronounced effects in the first 4 days). In these studies, the female rodents were not treated with methadone, indicating paternally-mediated developmental toxicity. Specifically, methadone administered to the male rat prior to mating with methadone-naïve females resulted in decreased weight gain in progeny after weaning. The male progeny demonstrated reduced thymus weights, whereas the female progeny demonstrated increased adrenal weights. Behavioral testing of these male and female progeny revealed significant differences in behavioral tests compared to control animals, suggesting that paternal methadone exposure can produce physiological and behavioral changes in progeny in this model. Examination of uterine contents of methadone-naïve female mice bred to methadone-treated male mice (once a day for three consecutive days) indicated that methadone treatment produced an increase in the rate of preimplantation deaths in all post-meiotic states at 1 mg/kg/day or greater (0.04 times the HDD). Chromosome analysis revealed a dose-dependent increase in the frequency of chromosomal abnormalities at 1 mg/kg/day or greater.

Studies demonstrated that methadone treatment of male rats for 21 to 32 days prior to mating with methadone-naïve females did not produce any adverse effects, suggesting that prolonged methadone treatment of the male rat resulted in tolerance to the developmental toxicities noted in the progeny. Mechanistic studies in this rat model suggest that the developmental effects of “paternal” methadone on the progeny appear to be due to decreased testosterone production. These animal data mirror the reported clinical findings of decreased testosterone levels in human males on methadone maintenance therapy for opioid addiction and in males receiving chronic intraspinal opioids.

8.2 Lactation

Risk Summary
Based on two small clinical studies, methadone was present in low levels in human milk, but the exposed infants in these studies did not show adverse reactions. Based on an average milk consumption of

150 mL/kg/day, an infant would consume approximately 17.4 mcg/kg/day which is approximately 2% to 3% of the oral maternal dose. There have been rare case reports of sedation and respiratory depression in infants exposed to methadone through breast milk (see Data). Monitor infants exposed to Methadose through breast milk for excess sedation and respiratory depression. The developmental and health benefits of breastfeeding should be considered along with the mother’s clinical need for methadone and any potential adverse effects on the breastfed child from the drug or from the underlying maternal condition.

Data
In a study of ten breastfeeding women maintained on oral methadone doses of 10 to 80 mg/day, methadone concentrations from 50 to 570 mcg/L in milk were reported, which, in the majority of samples, were lower than maternal serum drug concentrations at steady state. Peak methadone levels in milk occur approximately 4 to 5 hours after an oral dose.

In a study of twelve breastfeeding women maintained on oral methadone doses of 20 to 80 mg/day, methadone concentrations from 39 to 232 mcg/L in milk were reported. Based on an average milk consumption of 150 mL/kg/day, an infant would consume approximately 17.4 mcg/kg/day, which is approximately 2% to 3% of the oral maternal dose. Methadone has been detected in very low plasma concentrations in some infants whose mothers were taking methadone.

8.3 Females and Males of Reproductive Potential

Infertility
The effect of METHADOSE on fertility is unknown. Use of opioids for an extended period of time may cause reduced fertility in females and males of reproductive potential. It is not known whether these effects on fertility are reversible [see Adverse Reactions (6), Clinical Pharmacology (12.2), Nonclinical Toxicology (13)]. Reproductive function in human males may be decreased by methadone treatment. Reductions in ejaculate volume and seminal vesicle and prostate secretions have been reported in methadone-treated individuals. In addition, reductions in serum testosterone levels and sperm motility, and abnormalities in sperm morphology have been reported.

In published animal studies, methadone produces a significant regression of sex accessory organs and testes of male mice and rats and administration of methadone to pregnant rats reduced fetal blood testosterone and androstenedione in male offspring [see Nonclinical Toxicology (13)].

8.4 Pediatric Use

The safety, effectiveness, and pharmacokinetics of methadone in pediatric patients below the age of 18 years have not been established.

8.5 Geriatric Use

Clinical studies of methadone did not include sufficient numbers of subjects aged 65 and over to determine whether they respond differently compared to younger subjects. Other reported clinical experience has not identified differences in responses between elderly and younger patients. In general, start elderly patients at the low end of the dosing range, taking into account the greater frequency of decreased hepatic, renal, or cardiac function and of concomitant disease or other drug therapy. Closely monitor elderly patients for signs of respiratory and central nervous system depression.

Methadone is known to be substantially excreted by the kidney, and the risk of adverse reactions to this drug may be greater in patients with impaired renal function. Because elderly patients are more likely to have decreased renal function, care should be taken in dose selection, and it may be useful to monitor renal function.

8.6 Hepatic Impairment

Methadone pharmacokinetics have not been extensively evaluated in patients with hepatic insufficiency. Methadone is metabolized by hepatic pathways, therefore, patients with liver impairment may be at risk of increased systemic exposure to methadone after multiple dosing. Start these patients on lower doses and titrate slowly while carefully monitoring for signs of respiratory and central nervous system depression.

8.7 Renal Impairment

Methadone pharmacokinetics have not been extensively evaluated in patients with renal insufficiency. Since unmetabolized methadone and its metabolites are excreted in urine to a variable degree, start these patients on lower doses and with longer dosing intervals and titrate slowly while carefully monitoring for signs of respiratory and central nervous system depression.

9 DRUG ABUSE AND DEPENDENCE

9.1 Controlled Substance

METHADOSE contains methadone, a Schedule II opioid agonist.

9.2 Abuse

METHADOSE contains methadone, a substance with a high potential for abuse similar to other opioids including fentanyl, hydrocodone, hydromorphone, morphine, oxycodone, oxymorphone, and tapentadol. METHADOSE can be abused and is subject to misuse, addiction, and criminal diversion [see Warnings and Precautions (5.5)].

Prescription drug abuse is the intentional non-therapeutic use of a prescription drug, even once, for its rewarding psychological or physiological effects.

Drug addiction is a cluster of behavioral, cognitive, and physiological phenomena that develop after repeated substance use and includes: a strong desire to take the drug, difficulties in controlling its use, persisting in its use despite harmful consequences, a higher priority given to drug use than to other activities and obligations, increased tolerance, and sometimes a physical withdrawal.

“Drug-seeking” behavior is very common in persons with substance use disorders. Drug-seeking tactics include emergency calls or visits near the end of office hours, refusal to undergo appropriate examination, testing or referral, repeated “loss” of prescriptions, tampering with prescriptions, and reluctance to provide prior medical records or contact information for other treating healthcare provider(s). “Doctor shopping” (visiting multiple prescribers to obtain additional prescriptions) is common among people who abuse opioids and people suffering from untreated addiction. Abuse and addiction are separate and distinct from physical dependence and tolerance. Healthcare providers should be aware that addiction may not be accompanied by concurrent tolerance and symptoms of physical dependence in all people with substance use disorders. In addition, abuse of opioids can occur in the absence of true addiction.

METHADOSE, like other opioids, can be diverted for non-medical use into illicit channels of distribution. Careful record-keeping of prescribing information, including quantity and frequency as required by state and federal law, is strongly advised.

Proper assessment and selection of the patient, proper prescribing practices, periodic re-evaluation of therapy, and proper dispensing and storage are appropriate measures that help to limit abuse of opioid drugs.

Risks Specific to METHADOSE
Abuse of methadone poses a risk of overdose and death. This risk is increased with concurrent abuse of methadone with alcohol and other substances. METHADOSE is intended for oral use only and must not be injected. Parenteral drug abuse is commonly associated with transmission of infectious diseases such as hepatitis and HIV.

METHADOSE, when used for the treatment of opioid addiction in detoxification or maintenance programs, may be dispensed only by opioid treatment programs certified by the Substance Abuse and Mental Health Services Administration (and agencies, practitioners, and institutions by formal agreements with the program sponsor).

9.3 Dependence

Both tolerance and physical dependence can develop during chronic opioid therapy. Tolerance is the need for increasing doses of opioids to maintain a defined effect (in the absence of disease progression or other external factors). Tolerance may occur to both the desired and undesired effects of drugs, and may develop at different rates for different effects.

Physical dependence results in withdrawal symptoms after abrupt discontinuation or significant dose reduction of a drug. Withdrawal is also precipitated through the administration of drugs with opioid antagonist activity (e.g., naloxone, nalmefene) or mixed agonist/antagonist analgesics (e.g., pentazocine, butorphanol, nalbuphine), or partial agonists (e.g., buprenorphine). Physical dependence may not occur to a clinically significant degree until after several days to weeks of continued opioid usage. Physical dependence is expected during opioid agonist therapy of opioid addiction.

METHADOSE should not be rapidly reduced or abruptly discontinued [see Dosage and Administration (2.6, 2.7)]. If METHADOSE is rapidly reduced or abruptly discontinued in a physically-dependent patient, a withdrawal syndrome may occur. Some or all of the following can characterize this syndrome: restlessness, lacrimation, rhinorrhea, yawning, perspiration, chills, myalgia, and mydriasis. Other symptoms also may develop, including irritability, anxiety, backache, joint pain, weakness, abdominal cramps, insomnia, nausea, anorexia, vomiting, diarrhea, or increased blood pressure, respiratory rate, or heart rate [see Dosage and Administration (2.6)].

Neonatal opioid withdrawal syndrome (NOWS) is an expected and treatable outcome of prolonged use of opioids during pregnancy [see Warnings and Precautions (5.6)].

10 OVERDOSAGE

Clinical Presentation
Acute overdosage with methadone can be manifested by respiratory depression somnolence progressing to stupor or coma, skeletal-muscle flaccidity, cold and clammy skin, constricted pupils, and, in some cases, pulmonary edema, bradycardia, hypotension, hypoglycemia, partial or complete airway obstruction, atypical snoring, and death. Marked mydriasis rather than miosis may be seen with hypoxia in overdose situations [see Clinical Pharmacology (12.2)]. In severe overdosage, particularly by the intravenous route, apnea, circulatory collapse, cardiac arrest, and death may occur.

Methadone overdosage is associated with rhabdomyolysis. Seek medical attention, especially if abuse/misuse results in prolonged immobilization. Toxic leukoencephalopathy has been reported after opioid overdose, and can present hours, days, or weeks after apparent recovery from the initial intoxication. Hearing loss has been reported after methadone overdose, in some cases permanent.

Treatment of Overdose
In the case of overdose, priorities are the reestablishment of a patent and protected airway and institution of assisted or controlled ventilation, if needed. Employ other supportive measures (including oxygen and vasopressors) in the management of circulatory shock and pulmonary edema as indicated. Cardiac arrest or arrhythmias will require advanced life-support techniques.

For clinically significant respiratory or circulatory depression secondary to opioid overdose, administer an opioid overdose reversal agent such as naloxone or nalmefene.

Because the duration of opioid reversal is expected to be less than the duration of action of methadone, carefully monitor the patient until spontaneous respiration is reliably established. If the response to an opioid overdose reversal agent is suboptimal or not sustained, administer additional reversal agent as directed in the product’s prescribing information.

In an individual physically dependent on opioids, the administration of the usual dose of an opioid overdose reversal agent will precipitate an acute withdrawal syndrome. The severity of the withdrawal symptoms experienced will depend on the degree of physical dependence and the dose of the reversal agent administered. If a decision is made treat serious respiratory depression in the physically dependent patient, administration of the reversal agent should be initiated with care and by titration with smaller than usual doses of the reversal agent.

11 DESCRIPTION

METHADOSE™ (methadone hydrochloride, USP) oral concentrate contains methadone, an opioid agonist, and is available as a cherry-flavored liquid concentrate for oral administration. METHADOSE™ (methadone hydrochloride, USP) sugar-free oral concentrate is a dye-free, sugar-free, unflavored liquid concentrate of methadone hydrochloride for oral administration.

Methadone hydrochloride is chemically described as 6-(dimethylamino)-4,4-diphenyl-3-heptone hydrochloride. Methadone hydrochloride, USP is a fine white powder. It is very soluble in water, soluble in isopropanol and in chloroform, and practically insoluble in ether and in glycerine. It is present in METHADOSE as the racemic mixture. Methadone hydrochloride has a melting point of 235°C, a pKa of 8.25 in water at 20°C, a solution (1 part per 100) pH between 4.5 and 6.5, a partition coefficient of 117 at pH 7.4 in octanol/water and a molecular weight of 345.91. Its structural formula is C21H27NO•HCl.

Each liquid concentrate contains 10 mg of methadone hydrochloride (equivalent to 8.95 mg of methadone) per mL and the following inactive ingredients: artificial cherry flavor, citric acid anhydrous, FD&C Red No 40, D&C Red No 33, methylparaben, poloxamer 407, propylene glycol, propylparaben, purified water, sodium citrate dihydrate, sucrose.

Other ingredients of METHADOSE sugar-free oral concentrate: citric acid anhydrous, purified water, sodium benzoate.

12 CLINICAL PHARMACOLOGY

12.1 Mechanism of Action

Methadone hydrochloride is a mu-agonist; a synthetic opioid with multiple actions qualitatively similar to those of morphine, the most prominent of which involves the central nervous system and organs composed of smooth muscle. The methadone withdrawal syndrome, although qualitatively similar to that of morphine, differs in that the onset is slower, the course is more prolonged, and the symptoms are less severe.

Some data also indicate that methadone acts as an antagonist at the N-methyl-D-aspartate (NMDA) receptor. The contribution of NMDA receptor antagonism to methadone’s efficacy is unknown. Other NMDA receptor antagonists have been shown to produce neurotoxic effects in animals.

12.2 Pharmacodynamics

Effects on the Central Nervous System
Methadone produces respiratory depression by direct action on brain stem respiratory centers. The respiratory depression involves a reduction in the responsiveness of the brain stem respiratory centers to both increases in carbon dioxide tension and electrical stimulation.

Methadone causes miosis, even in total darkness. Pinpoint pupils are a sign of opioid overdose but are not pathognomonic (e.g., pontine lesions of hemorrhagic or ischemic origins may produce similar findings). Marked mydriasis rather than miosis may be seen due to hypoxia in overdose situations.

Some NMDA receptor antagonists have been shown to produce neurotoxic effects in animals.

Effects on the Gastrointestinal Tract and Other Smooth Muscle
Methadone causes a reduction in motility associated with an increase in smooth muscle tone in the antrum of the stomach and duodenum. Digestion of food in the small intestine is delayed and propulsive contractions are decreased. Propulsive peristaltic waves in the colon are decreased, while tone is increased to the point of spasm, resulting in constipation. Other opioid-induced effects may include a reduction in biliary and pancreatic secretions, spasm of sphincter of Oddi, transient elevations in serum amylase, and opioid-induced esophageal dysfunction (OIED).

Effects on the Cardiovascular System
Methadone produces peripheral vasodilation, which may result in orthostatic hypotension or syncope. Manifestations of histamine release and/or peripheral vasodilation may include pruritus, flushing, red eyes, sweating, and/or orthostatic hypotension.

Effects on the Endocrine System
Opioids inhibit the secretion of adrenocorticotropic hormone (ACTH), cortisol, and luteinizing hormone (LH) in humans. They also stimulate prolactin, growth hormone (GH) secretion, and pancreatic secretion of insulin and glucagon.

Chronic use of opioids may influence the hypothalamic-pituitary-gonadal axis, leading to androgen deficiency that may manifest as low libido, impotence, erectile dysfunction, amenorrhea, or infertility. The causal role of opioids in the clinical syndrome of hypogonadism is unknown because the various medical, physical, lifestyle, and psychological stressors that may influence gonadal hormone levels have not been adequately controlled for in studies conducted to date [see Adverse Reactions (6)].

Effects on the Immune System
Opioids have been shown to have a variety of effects on components of the immune system in in vitro and animal models. The clinical significance of these findings is unknown. Overall, the effects of opioids appear to be modestly immunosuppressive.

Concentration-Adverse Reaction Relationships
There is a relationship between increasing methadone plasma concentration and increasing frequency of dose-related opioid adverse reactions such as nausea, vomiting, CNS effects, and respiratory depression. In opioid-tolerant patients, the situation may be altered by the development of tolerance to opioid-related adverse reactions [see Dosage and Administration (2.4, 2.5, 2.6)].

12.3 Pharmacokinetics

Absorption
Following oral administration the bioavailability of methadone ranges between 36% to 100% and peak plasma concentrations are achieved between 1 and 7.5 hours. Dose proportionality of methadone pharmacokinetics is not known. However, after administration of daily oral doses ranging from 10 to 225 mg, the steady-state plasma concentrations ranged between 65 to 630 ng/mL and the peak concentrations ranged between 124 to 1255 ng/mL. Effect of food on the bioavailability of methadone has not been evaluated.

Distribution
Methadone is a lipophilic drug and the steady-state volume of distribution ranges between 1.0 to 8.0 L/kg. In plasma, methadone is predominantly bound to α1-acid glycoprotein (85% to 90%). Methadone is secreted in saliva, breast milk, amniotic fluid and umbilical cord plasma.

Elimination
Metabolism
Methadone is primarily metabolized by N-demethylation to an inactive metabolite, 2-ethylidene-1,5-dimethyl-3,3-diphenylpyrrolidene (EDDP). Cytochrome P450 enzymes, primarily CYP3A4, CYP2B6, CYP2C19, CYP2C9 and CYP2D6, are responsible for conversion of methadone to EDDP and other inactive metabolites, which are excreted mainly in the urine.

Excretion
The elimination of methadone is mediated by extensive biotransformation, followed by renal and fecal excretion. Published reports indicate that after multiple dose administration the apparent plasma clearance of methadone ranged between 1.4 and 126 L/h, and the terminal half-life (T1/2) was highly variable and ranged between 8 and 59 hours in different studies. Methadone is a basic (pKa=9.2) compound and the pH of the urinary tract can alter its disposition in plasma. Urine acidification has been shown to increase renal elimination of methadone. Forced diuresis, peritoneal dialysis, hemodialysis, or charcoal hemoperfusion have not been established as beneficial for increasing the elimination of methadone or its metabolites. Also, since methadone is lipophilic, it has been known to persist in the liver and other tissues. The slow release from the liver and other tissues may prolong the duration of methadone action despite low plasma concentrations.

Drug Interaction Studies
Cytochrome P450 Interactions
Methadone undergoes hepatic N-demethylation by cytochrome P450 isoforms, principally CYP3A4, CYP2B6, CYP2C19, CYP2C9 and CYP2D6. Coadministration of methadone with CYP inducers may result in more rapid metabolism and decreased effects of methadone, whereas administration with CYP inhibitors may reduce metabolism and potentiate methadone’s effects. Pharmacokinetics of methadone may be unpredictable when coadministered with drugs that are known to both induce and inhibit CYP enzymes. Although anti-retroviral drugs such as efavirenz, nelfinavir, nevirapine, ritonavir, and lopinavir+ritonavir combination are known to inhibit some CYPs, they are shown to reduce the plasma levels of methadone, possibly due to their CYP induction activity [see Drug Interactions (7)].

Cytochrome P450 Inducers
The following drug interactions were reported following coadministration of methadone with known inducers of cytochrome P450 enzymes:

- Rifampin: In patients well-stabilized on methadone, concomitant administration of rifampin resulted in a marked reduction in serum methadone levels and a concurrent appearance of withdrawal symptoms.
- Phenytoin: In a pharmacokinetic study with patients on methadone maintenance therapy, phenytoin administration (250 mg twice daily initially for 1 day followed by 300 mg daily for 3 to 4 days) resulted in an approximately 50% reduction in methadone exposure and withdrawal symptoms occurred concurrently. Upon discontinuation of phenytoin, the incidence of withdrawal symptoms decreased and methadone exposure increased to a level comparable to that prior to phenytoin administration.
- St. John’s Wort, Phenobarbital, Carbamazepine: Administration of methadone with other CYP3A4 inducers may result in withdrawal symptoms.

Cytochrome P450 Inhibitors

- Voriconazole: Voriconazole can inhibit the activity of CYP3A4, CYP2C9 and CYP2C19. Repeat dose administration of oral voriconazole (400 mg every 12 hours for 1 day, then 200 mg every 12 hours for 4 days) increased the Cmax and AUC of (R)-methadone by 31% and 47%, respectively, in subjects receiving a methadone maintenance dose (30 to 100 mg daily). The Cmax and AUC of (S)-methadone increased by 65% and 103%, respectively. Increased plasma concentrations of methadone have been associated with toxicity, including QT prolongation. Frequent monitoring for adverse events and toxicity related to methadone is recommended during coadministration. Dose reduction of methadone may be needed [see Drug Interactions (7)].

Anti-Retroviral Agents
Although anti-retroviral drugs such as efavirenz, nelfinavir, nevirapine, ritonavir, and lopinavir+ritonavir combination are known to inhibit CYPs, they are shown to reduce the plasma levels of methadone, possibly due to their CYP induction activity.

- Abacavir, Amprenavir, Efavirenz, Nelfinavir, Nevirapine, Ritonavir, Lopinavir+Ritonavir Combination: Coadministration of these anti-retroviral agents resulted in increased clearance or decreased plasma levels of methadone.
- Didanosine and Stavudine: Experimental evidence demonstrated that methadone decreased the area under the concentration-time curve (AUC) and peak levels for didanosine and stavudine, with a more significant decrease for didanosine. Methadone disposition was not substantially altered.
- Zidovudine: Experimental evidence demonstrated that methadone increased the AUC of zidovudine which could result in toxic effects.

13 NONCLINICAL TOXICOLOGY

13.1 Carcinogenesis, Mutagenesis, Impairment of Fertility

Carcinogenesis
The results of carcinogenicity assessment in B6C2F1 mice and Fischer 344 rats following dietary administration of two doses of methadone HCl have been published. Mice consumed 15 mg/kg/day or 60 mg/kg/day methadone for two years. These doses were approximately 0.6 and 2.5 times a human daily oral dose of 120 mg/day on a body surface area basis (HDD). There was a significant increase in pituitary adenomas in female mice treated with 15 mg/kg/day but not with 60 mg/kg/day. Under the conditions of the assay, there was no clear evidence for a treatment-related increase in the incidence of neoplasms in male rats. Due to decreased food consumption in males at the high dose, male rats consumed 16 mg/kg/day and 28 mg/kg/day of methadone for two years. These doses were approximately 1.3 and 2.3 times the HDD. In contrast, female rats consumed 46 mg/kg/day or 88 mg/kg/day for two years. These doses were approximately 3.7 and 7.1 times the HDD. Under the conditions of the assay, there was no clear evidence for a treatment-related increase in the incidence of neoplasms in either male or female rats.

Mutagenesis
There are several published reports on the potential genetic toxicity of methadone. Methadone tested positive in the in vivo mouse dominant lethal assay and the in vivo mammalian spermatogonial chromosome aberration test. Additionally, methadone tested positive in the E. coli DNA repair system and Neurospora crassa and mouse lymphoma forward mutation assays. In contrast, methadone tested negative in tests for chromosome breakage and disjunction and sex-linked recessive lethal gene mutations in germ cells of Drosophila using feeding and injection procedures.

Impairment of Fertility
Published animal studies provide additional data indicating that methadone treatment of males can alter reproductive function. Methadone produces decreased sexual activity (mating) of male rats at 10 mg/kg/day (corresponding to 0.3 times the human daily oral dose of 120 mg/day based on body surface area). Methadone also produces a significant regression of sex accessory organs and testes of male mice and rats at 0.2 and 0.8 times the HDD, respectively. Methadone treatment of pregnant rats from Gestation Day 14 to 19 reduced fetal blood testosterone and androstenedione in males. Decreased serum levels of testosterone were observed in male rats that were treated with methadone (1.3 to 3.3 mg/kg/day for 14 days, corresponding to 0.1 to 0.3 times the HDD) or 10 to 15 mg/kg/day for 10 days (0.8 to 1.2 times the HDD).

16 HOW SUPPLIED/STORAGE AND HANDLING

METHADOSE™ (methadone hydrochloride, USP) oral concentrate 10 mg per mL is supplied as a red, cherry-flavored liquid concentrate.

1-Liter Bottle................ NDC 0406-0527-10

METHADOSE™ (methadone hydrochloride, USP) sugar-free oral concentrate 10 mg per mL is supplied as a dye-free, sugar-free, unflavored clear liquid concentrate.

1-Liter Bottle................ NDC 0406-8725-10

Dispense in tight containers, protected from light. Store at 20° to 25°C (68° to 77°F) [see USP Controlled Room Temperature].

Store METHADOSE securely and dispose of properly [see Patient Counseling Information (17)].

17 PATIENT COUNSELING INFORMATION

Life-Threatening Respiratory Depression
Discuss the risk of respiratory depression with patients, explaining that the risk is greatest when starting METHADOSE or when the dose is increased.

Educate patients and caregivers on how to recognize respiratory depression and emphasize the importance of calling 911 or getting emergency medical help right away in the event of a known or suspected overdose [see Warnings and Precautions (5.1)].

Patient Access to an Opioid Overdose Reversal Agent for the Emergency Treatment of Opioid Overdose

Inform patients and caregivers about opioid overdose reversal agents (e.g., naloxone, nalmefene) and discuss the importance of having access to an opioid overdose reversal agent. Because patients being treated with methadone may be at risk for opioid overdose during initiation or titration, or in the case of relapse to illicit use, discuss the importance of having access to an opioid overdose reversal agent. Also discuss the importance of having access to an opioid overdose reversal agent if the patient has household members (including children) or other close contacts at risk for accidental ingestion or opioid overdose.

Discuss with the patient the options for obtaining an opioid overdose reversal agent (e.g., prescription, over-the-counter (some products), or as part of a community-based program) [see Dosage and Administration (2.3), Warnings and Precautions (5.1)].

There are important differences among the opioid overdose reversal agents. Be familiar with these differences, as outlined in the approved labeling for those products, prior to recommending or prescribing such an agent.

Educate patients and caregivers on how to recognize the signs and symptoms of an opioid overdose.

Explain to patients and caregivers that effects of opioid overdose reversal agents like naloxone and nalmefene are temporary, and that they must call 911 or get emergency medical help right away in all cases of known or suspected opioid overdose, even if an opioid overdose reversal agent is administered. Repeat administration may be necessary, particularly for overdose involving METHADOSE [see Dosage and Administration (2.3), Warnings and Precautions (5.1), Overdosage (10)].

Advise patients and caregivers:

- how to treat with an opioid overdose reversal agent in the event of an opioid overdose.
- to tell family and friends about their opioid overdose reversal agent, and to keep it in a place where family and friends can access it in an emergency.
- to read the Patient Information (or other educational material) that will come with their opioid overdose reversal agent. Emphasize the importance of doing this before an opioid emergency happens, so the patient and caregiver will know what to do.

Interactions with Benzodiazepines and Other CNS Depressants
Inform patients and caregivers that potentially fatal additive effects may occur if METHADOSE is used with benzodiazepines or other CNS depressants (e.g., alcohol, non-benzodiazepine sedative/hypnotics, anxiolytics, tranquilizers, muscle relaxants, general anesthetics, antipsychotics, gabapentinoids [gabapentin or pregabalin], and other opioids), and not to use these concomitantly unless supervised by a healthcare provider [see Warnings and Precautions (5.2), Drug Interactions (7)].

Symptoms of Arrhythmia
Instruct patients to seek medical attention immediately if they experience symptoms suggestive of an arrhythmia (such as palpitations, near syncope, or syncope) when taking METHADOSE [see Warnings and Precautions (5.3)].

Accidental Ingestion
Inform patients that accidental ingestion, especially by children, may result in respiratory depression or death [see Warnings and Precautions (5.4)]. Instruct patients to take steps to store METHADOSE securely. Advise patients to dispose of unused METHADOSE by flushing down the toilet.

Abuse Potential
Inform patients that METHADOSE contains methadone, a Schedule II controlled substance that is subject to abuse [see Warnings and Precautions (5.5)]. Instruct patients not to share METHADOSE with others and to take steps to protect METHADOSE from theft or misuse.

Important Administration Instructions [see Dosage and Administration (2)]
Instruct patients how to properly take METHADOSE, including the following:

- METHADOSE is for oral administration only. The preparation must not be injected.
- Inform patients that METHADOSE should be taken only as directed to reduce the risk of life-threatening adverse reactions (e.g., respiratory depression), and the dose should not be adjusted without consulting a physician or other healthcare professional.
- Reassure patients initiating treatment with METHADOSE for opioid dependence that the dose of methadone will “hold” for longer periods of time as treatment progresses.
- Apprise patients seeking to discontinue treatment with methadone for opioid dependence of the high risk of relapse to illicit drug use associated with discontinuation of METHADOSE maintenance treatment.
- Advise patients not to discontinue METHADOSE without first discussing the need for a tapering regimen with the prescriber.

Serotonin Syndrome
Inform patients that METHADOSE could cause a rare but potentially life-threatening condition resulting from concomitant administration of serotonergic drugs. Warn patients of the symptoms of serotonin syndrome and to seek medical attention right away if symptoms develop. Instruct patients to inform their physicians if they are taking, or plan to take, serotonergic medications [see Warnings and Precautions (5.9), Drug Interactions (7)].

MAOI Interaction
Inform patients to avoid taking METHADOSE while using any drugs that inhibit monoamine oxidase. Patients should not start MAOIs while taking METHADOSE [see Drug Interactions (7)].

Adrenal Insufficiency
Inform patients that METHADOSE could cause adrenal insufficiency, a potentially life-threatening condition. Adrenal insufficiency may present with non-specific symptoms and signs such as nausea, vomiting, anorexia, fatigue, weakness, dizziness, and low blood pressure. Advise patients to seek medical attention if they experience a constellation of these symptoms [see Warnings and Precautions (5.10)].

Anaphylaxis
Inform patients that anaphylaxis has been reported with ingredients contained in METHADOSE. Advise patients how to recognize such a reaction and when to seek medical attention [see Adverse Reactions (6)].

Neonatal Opioid Withdrawal
Advise women that if they are pregnant while being treated with METHADOSE, the baby may have signs of withdrawal at birth and that withdrawal is treatable [see Warnings and Precautions (5.6), Use in Specific Populations (8.1)].

Lactation
Advise women who are breastfeeding to monitor the infant for increased sleepiness (more than usual), difficulty breathing or limpness. Instruct nursing mothers using METHADOSE to watch for signs of methadone toxicity in their infants, which include increased sleepiness (more than usual), difficulty breastfeeding, breathing difficulties, or limpness. Instruct nursing mothers to talk to their baby’s healthcare provider immediately if they notice these signs. If they cannot reach the healthcare provider right away, instruct them to take the baby to the emergency room or call 911 (or local emergency services) [see Use in Specific Populations (8.2)].

Infertility
Advise patients that use of opioids, such as METHADOSE, for an extended period of time may cause reduced fertility. It is not known whether these effects on fertility are reversible [see Use in Specific Populations (8.3)].

Constipation
Advise patients of the potential for severe constipation, including management instructions and when to seek medical attention [see Adverse Reactions (6), Clinical Pharmacology (12.2)].

Hypoglycemia
Inform patients that methadone may cause hypoglycemia. Instruct patients how to recognize the symptoms of low blood glucose and to contact their health care provider if these symptoms occur [see Warnings and Precautions (5.17)].

Mallinckrodt, the “M” brand mark, the Mallinckrodt Pharmaceuticals logo and other brands are trademarks of a Mallinckrodt company.

© 2025 Mallinckrodt.

SpecGx LLC
Webster Groves, MO 63119 USA
Made in USA

Mallinckrodt™
Pharmaceuticals

PRINCIPAL DISPLAY PANEL - Methadose™ Oral Concentrate 1 Liter Bottle Label

NDC 0406-0527-10

1 Liter (1000 mL)

Methadose™ Oral Concentrate
(methadone hydrochloride oral concentrate USP)

CII

10 mg per mL

Each milliliter contains:

Methadone Hydrochloride ............................. 10 mg

Methadose™ also contains Artificial Cherry Flavor, Citric Acid, FD&C Red 40, D&C Red 33, Methylparaben, Poloxamer 407, Propylene Glycol, Propylparaben, Purified Water, Sodium Citrate and Sucrose.

Rx only

DO NOT USE IF SEAL AROUND BOTTLE CAP IS BROKEN OR MISSING.

USUAL DOSE: To be determined by the physician; to be diluted with water or other liquid to 30 mL (1 fl. oz.) or more before oral administration.

Preserve in tight containers, protected from light. Store at 20° to 25°C (68° to 77°F) [see USP Controlled Room Temperature].

Mallinckrodt™

GTIN: 00304060527102

L00M07 Rev 10/2018

SpecGx LLC, Webster Groves, MO 63119 USA

Made in USA

PRINCIPAL DISPLAY PANEL - Methadose™ Sugar-Free Oral Concentrate 1 Liter Bottle Label

NDC 0406-8725-10

1 Liter (1000 mL)

Methadose™ Sugar-Free Oral Concentrate
(methadone hydrochloride oral concentrate USP)
dye-free, sugar-free, unflavored

CII

10 mg per mL

Each milliliter contains:
Methadone Hydrochloride ............................. 10 mg

Methadose™ Sugar-Free Oral Concentrate also contains Citric Acid Anhydrous, Purified Water and Sodium Benzoate.

Rx only

DO NOT USE IF SEAL AROUND BOTTLE CAP IS BROKEN OR MISSING.

USUAL DOSE: To be determined by the physician; to be diluted with water or other liquid to 30 mL (1 fl. oz.) or more before oral administration.

Preserve in tight containers, protected from light. Store at 20° to 25°C (68° to 77°F) [see USP Controlled Room Temperature].

Mallinckrodt™

GTIN: 00304068725104

L00M22 Rev 10/2018

SpecGx LLC, Webster Groves, MO 63119 USA

Made in USA